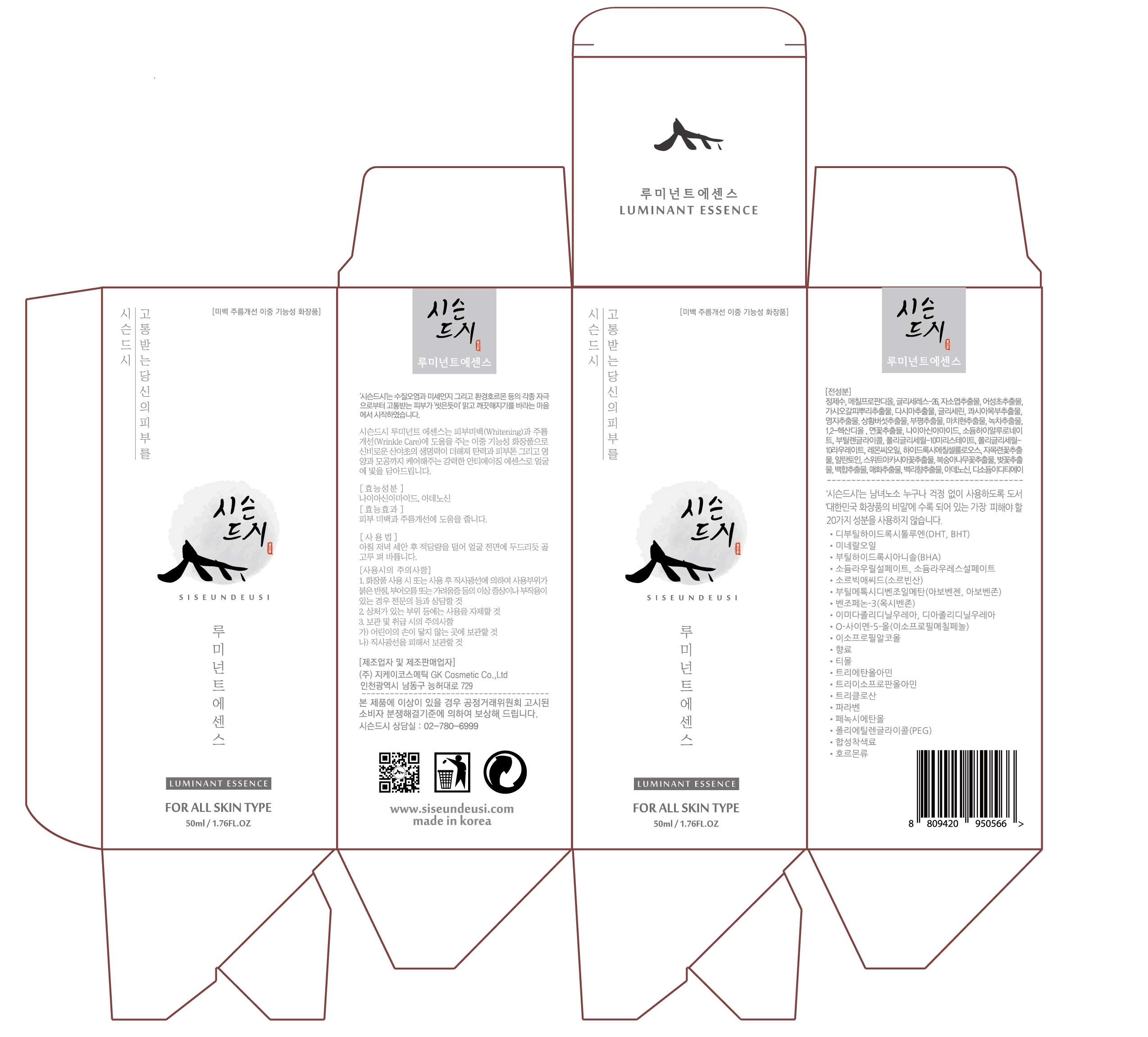 DRUG LABEL: SISEUNDEUSI LUMINANT ESSENCE
NDC: 70098-0011 | Form: LIQUID
Manufacturer: GK COSMETIC CO., LTD.
Category: otc | Type: HUMAN OTC DRUG LABEL
Date: 20170612

ACTIVE INGREDIENTS: NIACINAMIDE 2.1 g/100 mL; ADENOSINE 0.045 g/100 mL
INACTIVE INGREDIENTS: BUTYLENE GLYCOL; GLYCERIN

Drug Facts

ACTIVE INGREDIENT

Niacinamide, Adenosine

INACTIVE INGREDIENT

Methylpropanediol, Glycereth-26, Perilla Frutescens Leaf Extract, Glycerin, Portulaca Oleracea Extract, etc.

PURPOSE

Whitening, Anti-Wrinkle

keep out of reach of the children

INDICATIONS AND USAGE

Siseundeusi’s Luminant essence is a functional cosmetic which is effective for whitening and wrinkle care. The ingredient of Luminant essence, Miraculous Native Grass extract has strong anti-aging effect; it helps to improve your skin’s elasticity and skin tones and gives your skin nutrients and takes cares of your pores; it brings brightness on your skin.

WARNINGS

1. Do not use in the following cases(Eczema and scalp wounds)
2.Side Effects
1)Due to the use of this druf if rash, irritation, itching and symptopms of hypersnesitivity occur dicontinue use and consult your phamacisr or doctor
3.General Precautions
1)If in contact with the eyes, wash out thoroughty with water If the symptoms are servere, seek medical advice immediately
2)This product is for exeternal use only. Do not use for internal use
4.Storage and handling precautions
1)If possible, avoid direct sunlight and store in cool and area of low humidity
2)In order to maintain the quality of the product and avoid misuse
3)Avoid placing the product near fire and store out in reach of children

DOSAGE AND ADMINISTRATION

for external use only